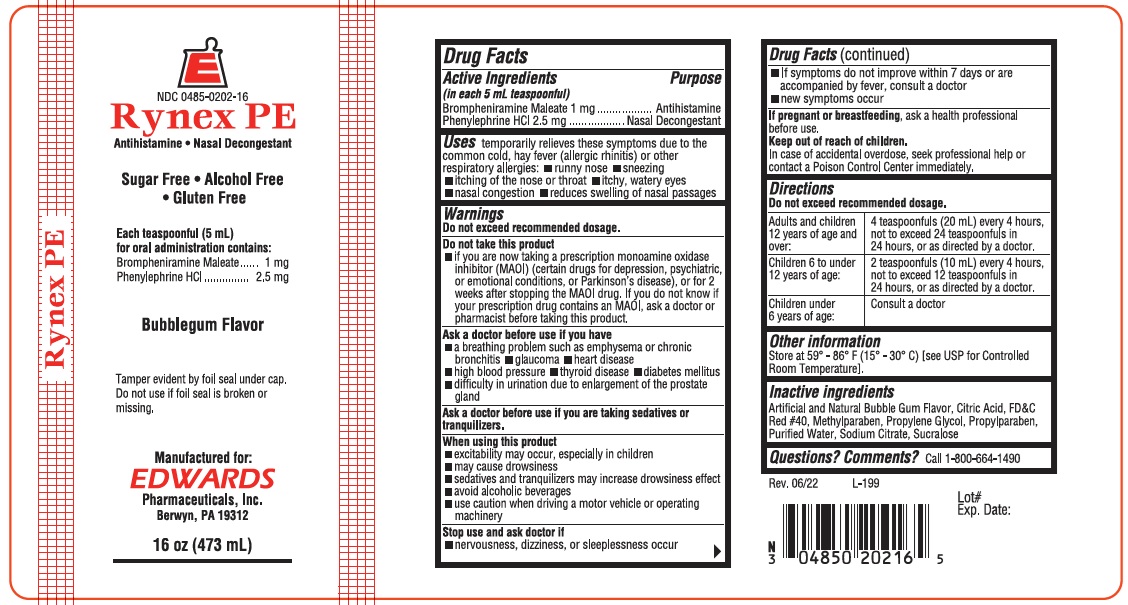 DRUG LABEL: RYNEX PE
NDC: 0485-0202 | Form: LIQUID
Manufacturer: EDWARDS PHARMACEUTICALS, INC.
Category: otc | Type: HUMAN OTC DRUG LABEL
Date: 20251230

ACTIVE INGREDIENTS: BROMPHENIRAMINE MALEATE 1 mg/5 mL; PHENYLEPHRINE HYDROCHLORIDE 2.5 mg/5 mL
INACTIVE INGREDIENTS: SUCRALOSE; PROPYLPARABEN; PROPYLENE GLYCOL; WATER; SODIUM CITRATE, UNSPECIFIED FORM; CITRIC ACID MONOHYDRATE; FD&C RED NO. 40; METHYLPARABEN

ED-RynexPE 0202

Drug Facts

ACTIVE INGREDIENT

Active Ingredients (in each 5 nil teaspoonful) | Purpose
Brompheniramine Maleate 1 mg | Antihistamine
Phenylephrine HCl 2.5 mg | Nasal Decongestant

Uses

temporarily relieves these symptoms due to the common cold, hay fever (allergic rhinitis) or other respiratory allergies:

- runny nose
- sneezing
- itching of the nose or throat
- itchy, watery eyes
- nasal congestion
- reduces swelling of nasal passage

Warnings

Do not exceed recommended dosage.

Do not take this product

- if you are now taking a prescription monoamine oxidase inhibitor (MA0I) (certain drugs for depression, psychiatric, or emotional conditions, or Parkinson's disease), or for 2 weeks after stopping the MAOI drug. If you do not know if your prescription drug contains an MAOI, ask a doctor or pharmacist before taking this product.

Ask a doctor before use if you have

- a breathing problem such as emphysema or chronic bronchitis
- glaucoma
- heart disease
- high blood pressure
- thyroid disease
- diabetes mellitus
- difficulty in urination due to enlargement of the prostate gland

Ask a doctor before use if you are taking sedatives or tranquilizers.

When using this product

- excitability may occur, especially in children
- may cause drowsiness
- sedalives and tranquilizers may increase drowsiness effect
- avoid alcoholic beverages
- use caution when driving a motor vehicle or operating machinery

Stop use and ask doctor if

- nervousness, dizziness, or sleeplessness occur
- If symptoms do not improve within 7 days or are accompanied by fever, consult a doctor
- new symptoms occur

PREGNANCY OR BREAST FEEDING

If pregnant or breast feeding, ask a health professional before use.

Keep out of reach of children.

In case of accidental overdose, seek professional help or contact a Poison Control Center immediately.

Directions

Do not exceed recommended dosage.

Adults and children 12 years of age and over: | 4 teaspoonfuls (20 mL) every 4 hours, not to exceed 24 teaspoonfuls in 24 hours, or as directed by a doctor.
Children 6 to under 12 years of age: | 2 teaspoonfuls(10 mL) every 4 hours, not to exceed 1 teaspoonfuls in 24 hours, or as directed by a doctor.
Children under 6 years of age: | Consult a doctor

Other information

Store at 59° - 86° F (15° - 30° C) [see USP for Controlled Room Temperature].

Inactive ingredients

Artifical and natural Bubblegum Flavor, Citric Acid, FD&C Red #40, Methyl Paraben, methylparaben, Propylene Glycol, Propyl Paraben, Purified Water, Sodium citrate, Sucralose.

Questions Comments?

Call 1-800-664-1490

PRINCIPAL DISPLAY PANEL - 473 mL Bottle Label

Rynex PE

E

NDC 0485-0202-16

Rynex PE
Antihistamine • Nasal Decongestant

Sugar Free • Alcohol Free
• Gluten Free

Each teaspoonful (5 mL)
for oral administration contains:
Brompheniramine Maleate 1 mg
Phenylephrine HCl 2.5 mg

Bubblegum Flavor
FOR PROFESSIONAL USE ONLY

Tamper evident by foil seal under cap.
Do not use if foil seal is broken or
missing.

Manufactured for:
EDWARDS
Pharmaceuticals, Inc.
Ripley, MS 38663

16oz. (473 mL)